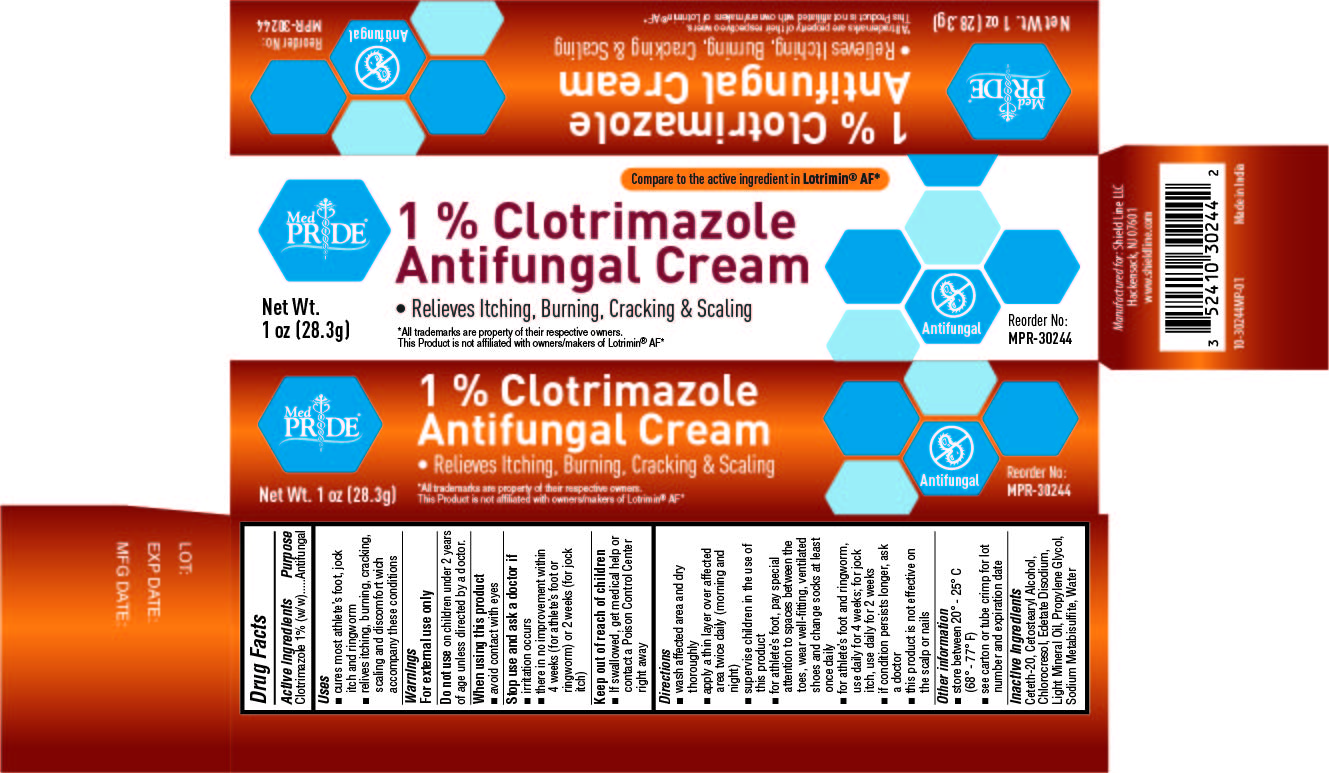 DRUG LABEL: Clotrimazole 1%
NDC: 52410-3024 | Form: CREAM
Manufacturer: Shield Line LLC
Category: otc | Type: HUMAN OTC DRUG LABEL
Date: 20250815

ACTIVE INGREDIENTS: CLOTRIMAZOLE 10 mg/1 g
INACTIVE INGREDIENTS: SODIUM METABISULFITE; PROPYLENE GLYCOL; CETOSTEARYL ALCOHOL; EDETATE DISODIUM; WATER; CHLOROCRESOL; LIGHT MINERAL OIL; CETETH-20

MedPride Clotrimazole USP, 1%

Drug Facts

Active ingredient

Clotrimazole 1% (w/w)

Purpose

Antifungal

Uses

- cures most athlete's foot, jock itch and ringworm
- relieves itching, burning, cracking, scaling and discomfort which accompany these conditions

Warnings

For external use only

Do not use on children under 2 years of age unless directed by a doctor.

When using this product

- avoid contact with eyes.

Stop use and ask a doctor if

- irritation occurs
- there is no improvement within 4 weeks (for athlete's foot or ringworm) or 2 weeks (for jock itch).

Keep out of reach of children. If swallowed, get medical help or contact a Poison Control Center right away.

Directions

- wash affected area and dry thoroughly
- apply a thin layer over affected area twice daily (morning and night)
- supervise children in the use of this product
- for athlete's foot, pay special attention to spaces between the toes, wear well-fitting, ventilated shoes and change socks at least once daily
- for athlete's foot and ringworm, use daily for 4 weeks; for jock itch, use daily for 2 weeks
- if condition persists longer, ask a doctor
- this product is not effective on the scalp or nails

Other information

- store between 20° - 25°C (68° - 77°F)
- see carton or tube crimp for lot number and expiration date

Inactive ingredients

Ceteth-20, Cetostearyl Alcohol, Chorocresol, Edetate Disodium, Light Mineral Oil, Propylene Glycol, Sodium Metabisulfite,Water